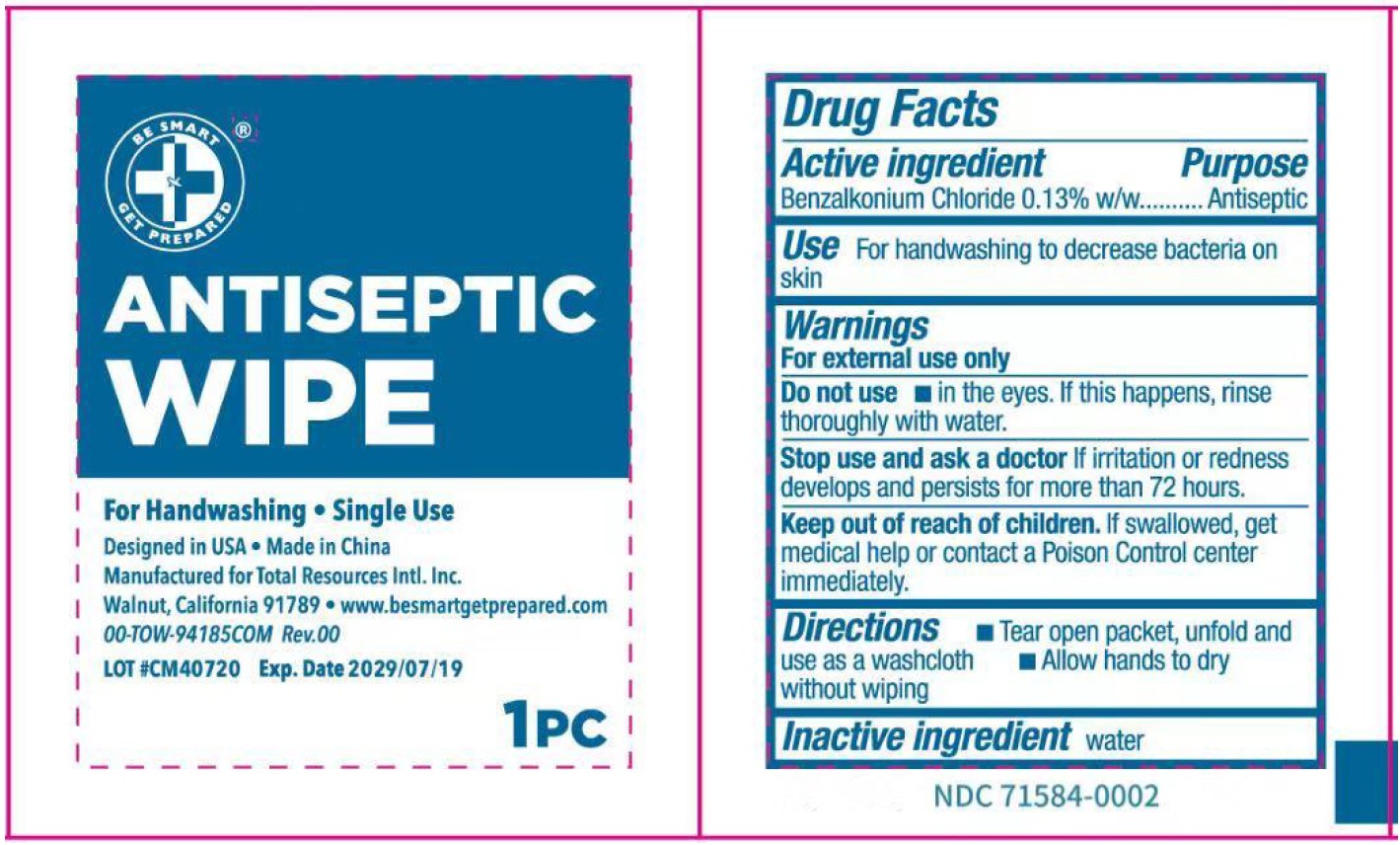 DRUG LABEL: ANTISEPTIC WIPE
NDC: 71584-0002 | Form: SWAB
Manufacturer: Guangdong Comfort Medical Products Co., Ltd.
Category: otc | Type: HUMAN OTC DRUG LABEL
Date: 20251019

ACTIVE INGREDIENTS: BENZALKONIUM CHLORIDE 0.13 g/100 g
INACTIVE INGREDIENTS: WATER

ACTIVE INGREDIENT

Benzalkonium chloride 0.13%

PURPOSE

First Aid Antiseptic

Keep out of reach of children, If swallowed, get medical help or contact a Poison Control Center right away.

INDICATIONS AND USAGE

Antiseptic cleansing of face, hands and body to decrease bacteria on skin without soap and water.

WARNINGS

For external use only.

DOSAGE AND ADMINISTRATION

Tear open packet, unfold and use as a washcloth. Allow hands to dry without wiping.

INACTIVE INGREDIENT

Water

ACTIVE INGREDIENT:
Benzalkonium chloride 0.13%
PURPOSE:
First Aid Antiseptic
USES:
Antiseptic cleansing of face, hands and body to decrease bacteria on skin without soap and water.
WARNINGS:
For external use only.
DO NOT USE:
in the eyes. Ifthis happens, rinse thoroughly with water.
STOP USE and ASK A DOCTOR:
If irritation or redness develop and persists for more than 72 hours.
CAUTION:
Keep out of reach of children, If swallowed, get medical help or contact a Poison Control Center right away.
DIRECTIONS:
Tear open packet, unfold and use as a washcloth. Allow hands to dry without wiping.
OTHER INFORMATION:
Store at room temperature.
INACTIVE INGREDIENTS:
water